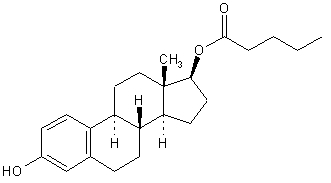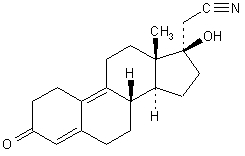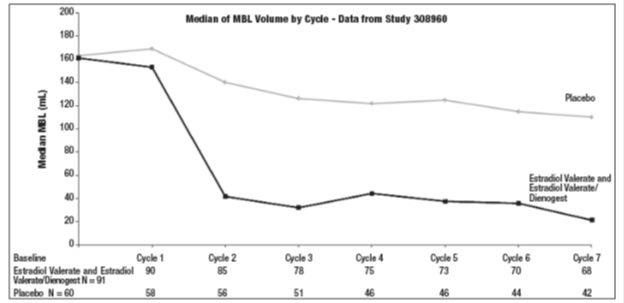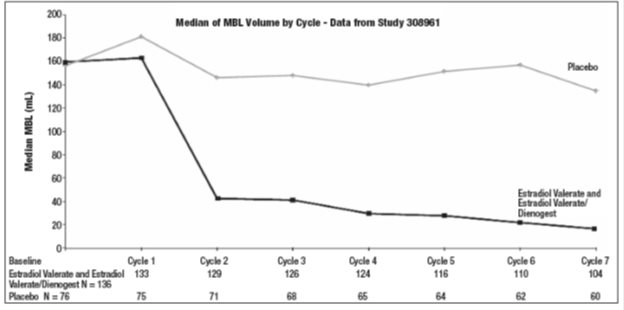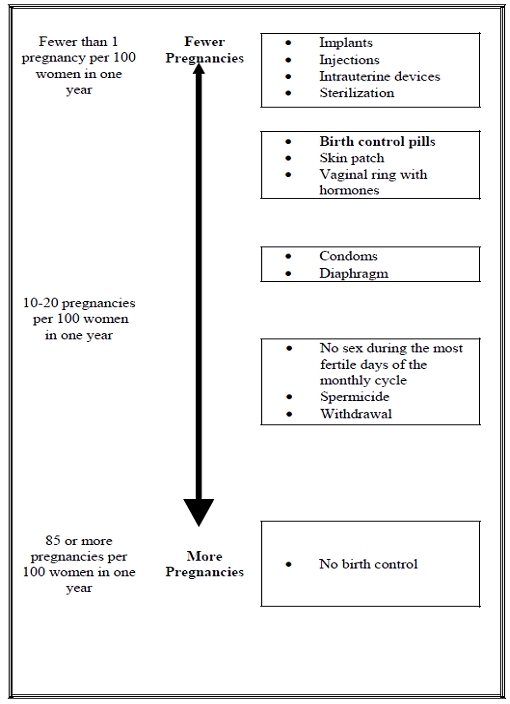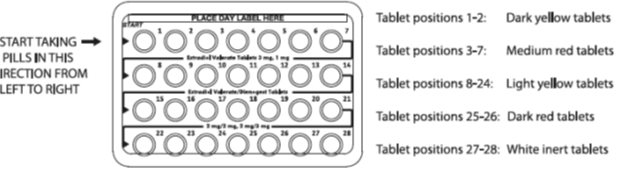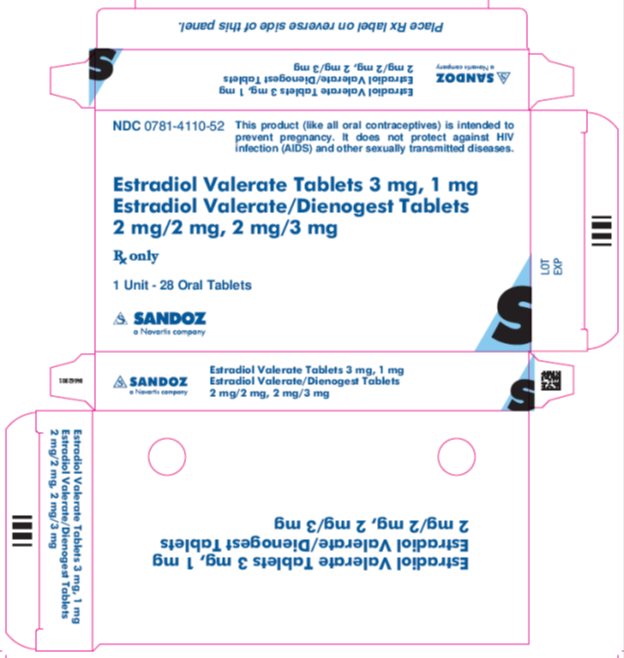 DRUG LABEL: Estradiol Valerate and Estradiol Valerate/Dienogest
NDC: 0781-4110 | Form: KIT | Route: ORAL
Manufacturer: Sandoz Inc
Category: prescription | Type: HUMAN PRESCRIPTION DRUG LABEL
Date: 20200121

ACTIVE INGREDIENTS: ESTRADIOL VALERATE 3 mg/1 1; ESTRADIOL VALERATE 2 mg/1 1; DIENOGEST 2 mg/1 1; ESTRADIOL VALERATE 2 mg/1 1; DIENOGEST 3 mg/1 1; ESTRADIOL VALERATE 1 mg/1 1
INACTIVE INGREDIENTS: FERRIC OXIDE YELLOW; LACTOSE MONOHYDRATE; POLYETHYLENE GLYCOL 6000; MAGNESIUM STEARATE; STARCH, CORN; POVIDONE K25; TALC; TITANIUM DIOXIDE; HYPROMELLOSE, UNSPECIFIED; FERRIC OXIDE RED; HYPROMELLOSE, UNSPECIFIED; LACTOSE MONOHYDRATE; POLYETHYLENE GLYCOL 6000; MAGNESIUM STEARATE; STARCH, CORN; POVIDONE K25; TALC; TITANIUM DIOXIDE; FERRIC OXIDE YELLOW; HYPROMELLOSE, UNSPECIFIED; LACTOSE MONOHYDRATE; POLYETHYLENE GLYCOL 6000; MAGNESIUM STEARATE; STARCH, CORN; POVIDONE K25; TALC; TITANIUM DIOXIDE; HYPROMELLOSE, UNSPECIFIED; LACTOSE MONOHYDRATE; POLYETHYLENE GLYCOL 6000; MAGNESIUM STEARATE; STARCH, CORN; TALC; TITANIUM DIOXIDE; POVIDONE K25; FERRIC OXIDE RED; HYPROMELLOSE, UNSPECIFIED; LACTOSE MONOHYDRATE; POLYETHYLENE GLYCOL 6000; MAGNESIUM STEARATE; STARCH, CORN; POVIDONE K25; TALC; TITANIUM DIOXIDE

HIGHLIGHTS OF PRESCRIBING INFORMATION

These highlights do not include all the information needed to use ESTRADIOL VALERATE AND ESTRADIOL VALERATE/DIENOGEST TABLETS safely and effectively. See full prescribing information for Estradiol Valerate and Estradiol Valerate/Dienogest.
ESTRADIOL VALERATE AND ESTRADIOL VALERATE/DIENOGESTTABLETS, for oral use
Initial U.S. Approval: 2010

WARNING: CIGARETTE SMOKING AND SERIOUS CARDIOVASCULAR EVENTS

See full prescribing information for complete boxed warning.

- Women over 35 years old who smoke should not use Estradiol Valerate and Estradiol Valerate/Dienogest . (4)
- Cigarette smoking increases the risk of serious cardiovascular events from combination oral contraceptive (COC) use. (4)

1 INDICATIONS AND USAGE

- Estradiol Valerate and Estradiol Valerate/Dienogest is an estrogen/progestin COC indicated for use by women to prevent pregnancy. (1)
- Treatment of heavy menstrual bleeding in women without organic pathology who choose to use an oral contraceptive as their method of contraception. (1.2)
- The efficacy of Estradiol Valerate and Estradiol Valerate/Dienogest in women with a body mass index (BMI) of
  >30 kg/m^2 has not been evaluated. (1, 8.8)

2 DOSAGE AND ADMINISTRATION

- Take one tablet daily by mouth at the same time every day. (2.1)
- Tablets must be taken in the order directed on the blister pack. (2.1)
- Do not skip or delay intake by more than 12 hours. (2.1)

3 DOSAGE FORMS AND STRENGTHS

Estradiol Valerate and Estradiol Valerate/Dienogest consists of 28 film-coated, unscored tablets in the following order (3):

- 2 dark yellow tablets each containing 3 mg estradiol valerate
- 5 medium red tablets each containing 2 mg estradiol valerate and 2 mg dienogest
- 17 light yellow tablets each containing 2 mg estradiol valerate and 3 mg dienogest
- 2 dark red tablets each containing 1 mg estradiol valerate
- 2 white tablets (inert)

4 CONTRAINDICATIONS

- A high risk of arterial or venous thrombotic diseases (4)
- Undiagnosed abnormal uterine bleeding (4)
- Breast cancer or other estrogen- or progestin-sensitive cancer (4)
- Liver tumors or liver disease (4)
- Pregnancy (4)

5 WARNINGS AND PRECAUTIONS

- Vascular risks: Stop Estradiol Valerate and Estradiol Valerate/Dienogest if a thrombotic event occurs. Stop Estradiol Valerate and Estradiol Valerate/Dienogest at least 4 weeks before and through 2 weeks after major surgery. Start Estradiol Valerate and Estradiol Valerate/Dienogest no earlier than 4 weeks after delivery, in women who are not breastfeeding. (5.1)
- Liver disease: Discontinue Estradiol Valerate and Estradiol Valerate/Dienogest if jaundice occurs. (5.3)
- High blood pressure: Do not prescribe Estradiol Valerate and Estradiol Valerate/Dienogest for women with uncontrolled hypertension or hypertension with vascular disease. (5.4)
- Carbohydrate and lipid metabolic effects: Monitor prediabetic and diabetic women taking Estradiol Valerate and Estradiol Valerate/Dienogest. Consider an alternate contraceptive method for women with uncontrolled dyslipidemia. (5.6)
- Headache: Evaluate significant change in headaches and discontinue Estradiol Valerate and Estradiol Valerate/Dienogest if indicated. (5.7)
- Uterine bleeding: Evaluate irregular bleeding or amenorrhea. (5.8)
- CYP3A4 induction: Women taking strong CYP3A4 inducers (for example, carbamazepine, phenytoin, rifampicin, and St. John’s wort) should not choose Estradiol Valerate and Estradiol Valerate/Dienogest as their oral contraceptive due to the possibility of decreased contraceptive efficacy. (5.13, 7.1)

6 ADVERSE REACTIONS

The most common adverse reactions (≥ 2%) in clinical trials for Estradiol Valerate and Estradiol Valerate/Dienogest are headaches, irregular uterine bleeding,headache (including migraines) 13%, breast tenderness,pain 7%, menstrual disorders 7%, nausea/ or vomiting, 6%, acne 4%, mood changes (3%) and increased weight. 3%. (6)

To report SUSPECTED ADVERSE REACTIONS, contact Bayer HealthCare Pharmaceuticals Inc. at 1-888-842-2937 or FDA at 1-800-FDA-1088 or www.fda.gov/medwatch

7 DRUG INTERACTIONS

Drugs or herbal products that induce certain enzymes (for example, CYP3A4) may decrease the effectiveness of COCs or increase breakthrough bleeding. Counsel patients to use a back-up or alternative method of contraception when enzyme inducers are used with COCs. (7.1)

8 USE IN SPECIFIC POPULATIONS

- Nursing mothers: Not recommended; can decrease milk production. (8.3)
- Body Mass Index: The safety and efficacy of Estradiol Valerate and Estradiol Valerate/Dienogest in women with a body mass index (BMI) of >30 kg/m^2 has not been evaluated. (8.8)

FULL PRESCRIBING INFORMATION

WARNING: CIGARETTE SMOKING AND SERIOUS CARDIOVASCULAR EVENTS

Cigarette smoking increases the risk of serious cardiovascular events from combination oral contraceptives (COC) use. This risk increases with age, particularly in women over 35 years of age, and with the number of cigarettes smoked. For this reason, COCs should not be used by women who are over 35 years of age and smoke. [See Contraindications (4).]

1 INDICATIONS AND USAGE

1.1 Oral Contraception

Estradiol Valerate and Estradiol Valerate/Dienogest is indicated for use by women to prevent pregnancy.

The efficacy of Estradiol Valerate and Estradiol Valerate/Dienogest in women with a body mass index (BMI) of > 30 kg/m^2 has not been evaluated.

1.2 Heavy Menstrual Bleeding

Estradiol Valerate and Estradiol Valerate/Dienogest is also indicated for the treatment of heavy menstrual bleeding in women without organic pathology who choose to use an oral contraceptive as their method of contraception [see Clinical Studies (14.2)].

2 DOSAGE AND ADMINISTRATION

2.1 How to Take Estradiol Valerate and Estradiol Valerate/Dienogest

To achieve maximum contraceptive effectiveness, Estradiol Valerate and Estradiol Valerate/Dienogest must be taken exactly as directed. Take one tablet by mouth at the same time every day. Tablets must be taken in the order directed on the blister pack. Tablets should not be skipped or intake delayed by more than 12 hours. For patient instructions for missed pills, see FDA-Approved Patient Labeling.

2.2 How to Start Estradiol Valerate and Estradiol Valerate/Dienogest

Instruct the patient to begin taking Estradiol Valerate and Estradiol Valerate/Dienogest on Day 1 of her menstrual cycle (that is, the first day of her menstrual bleeding). See FDA-Approved Patient Labeling. Instruct the patient to use a non-hormonal contraceptive as back-up during the first 9 days.

For postpartum women who do not breastfeed or after a second trimester abortion, start Estradiol Valerate and Estradiol Valerate/Dienogest no earlier than 4 weeks postpartum due to the increased risk of thromboembolism. If the patient starts on Estradiol Valerate and Estradiol Valerate/Dienogest postpartum and has not yet had a period, evaluate for possible pregnancy, and instruct her to use an additional method of contraception until she has taken Estradiol Valerate and Estradiol Valerate/Dienogest for 9 consecutive days. The possibility of ovulation and conception prior to initiation of medication should also be considered.

If the patient is switching from a combination hormonal method such as a:

  - Another pill
  - Vaginal ring
  - Patch
- Instruct her to take the first dark yellow pill on the first day of her withdrawal bleed. She should not continue taking the pills from her previous birth control pack. If she does not have a withdrawal bleed, rule out pregnancy before starting Estradiol Valerate and Estradiol Valerate/Dienogest.
- If she previously used a vaginal ring or transdermal patch, she should start using Estradiol Valerate and Estradiol Valerate/Dienogest on the day the ring or patch is removed.
- Instruct the patient to use a non-hormonal back-up method such as a condom or spermicide for the first 9 days.

If the patient is switching from a progestin-only method such as a:

  - Progestin-only pill
  - Implant
  - Intrauterine system
  - Injection
- Instruct her to take the first dark yellow pill on the day she would have taken her next progestin-only pill or on the day of removal of her implant or intrauterine system or on the day when she would have had her next injection.
- Instruct the patient to use a non-hormonal back-up method such as a condom or spermicide for the first 9 days.

2.3 Advice in Case of Gastrointestinal Disturbances

In case of severe vomiting or diarrhea, absorption may not be complete and additional contraceptive measures should be taken. If vomiting or diarrhea occurs within 3-4 hours after taking a colored tablet, this can be regarded as a missed tablet.

3 DOSAGE FORMS AND STRENGTHS

Estradiol Valerate and Estradiol Valerate/Dienogest (estradiol valerate and estradiol valerate/dienogest) tablets are available in blister packs.

Each blister pack contains 28 round, biconvex, film-coated tablets in the following order:

- 2 dark yellow tablets, with an embossed “DD” in a regular hexagon on one side, each containing 3 mg estradiol valerate
- 5 medium red tablets, with an embossed “DJ” in a regular hexagon on one side, each containing 2 mg estradiol valerate and 2 mg dienogest
- 17 light yellow tablets, with an embossed “DH” in a regular hexagon on one side, each containing 2 mg estradiol valerate and 3 mg dienogest
- 2 dark red tablets, with an embossed “DN” in a regular hexagon on one side, each containing 1 mg estradiol valerate
- 2 white tablets (inert), with an embossed “DT” in a regular hexagon on one side

4 CONTRAINDICATIONS

Do not prescribe Estradiol Valerate and Estradiol Valerate/Dienogest to women who are known to have the following:

- A high risk of arterial or venous thrombotic diseases. Examples include women who are known to:
  - Smoke, if over age 35 [see Boxed Warning and Warnings and Precautions (5.1)]
  - Have deep vein thrombosis or pulmonary embolism, now or in the past [see Warnings and Precautions (5.1)]
  - Have cerebrovascular disease [see Warnings and Precautions (5.1)]
  - Have coronary artery disease [see Warnings and Precautions (5.1)]
  - Have thrombogenic valvular or thrombogenic rhythm diseases of the heart (for example, subacute bacterial endocarditis with valvular disease, or atrial fibrillation) [see Warnings and Precautions (5.1)]
  - Have inherited or acquired hypercoagulopathies [see Warnings and Precautions (5.1)]
  - Have uncontrolled hypertension [see Warnings and Precautions (5.4)]
  - Have diabetes mellitus with vascular disease [see Warnings and Precautions (5.6)]
  - Have headaches with focal neurological symptoms or have migraine headaches with or without aura if over age 35 [see Warnings and Precautions (5.7)]
- Undiagnosed abnormal uterine bleeding [see Warnings and Precautions (5.8)]
- Breast cancer or other estrogen- or progestin-sensitive cancer, now or in the past [see Warnings and Precautions (5.2)]
- Liver tumors, benign or malignant, or liver disease [see Warnings and Precautions (5.3), Use in Specific Populations (8.7) and Clinical Pharmacology (12.3)].
- Pregnancy, because there is no reason to use COCs during pregnancy [see Warnings and Precautions (5.9) and Use in Specific Populations (8.1)].

5 WARNINGS AND PRECAUTIONS

5.1 Thromboembolic Disorders and Other Vascular Problems

Stop Estradiol Valerate and Estradiol Valerate/Dienogest if an arterial or venous thrombotic event (VTE) occurs.

The use of COCs increases the risk of venous thromboembolism. However, pregnancy increases the risk of venous thromboembolism as much or more than the use of COCs. The risk of VTE in women using COCs has been estimated to be 3 to 9 per 10,000 woman-years. The risk of VTE is highest during the first year of use. Data from a large, prospective cohort safety study of various COCs suggest that this increased risk, as compared to that in non-COC users, is greatest during the first 6 months of COC use. Data from this safety study indicate that the greatest risk of VTE is present after initially starting a COC or restarting (following a 4 week or greater pill-free interval) the same or a different COC.

Use of COCs also increases the risk of arterial thromboses such as strokes and myocardial infarctions, especially in women with other risk factors for these events.

The risk of thromboembolic disease due to oral contraceptives gradually disappears after COC use is discontinued.

If feasible, stop Estradiol Valerate and Estradiol Valerate/Dienogest at least 4 weeks before and through 2 weeks after major surgery or other surgeries known to have an elevated risk of thromboembolism.

Start Estradiol Valerate and Estradiol Valerate/Dienogest no earlier than 4 weeks after delivery, in women who are not breastfeeding. The risk of postpartum thromboembolism decreases after the third postpartum week, whereas the risk of ovulation increases after the third postpartum week.

COCs have been shown to increase both the relative and attributable risks of cerebrovascular events (thrombotic and hemorrhagic strokes), although, in general, the risk is greatest among older (>35 years of age), hypertensive women who also smoke. COCs also increase the risk for stroke in women with other underlying risk factors.

Oral contraceptives must be used with caution in women with cardiovascular disease risk factors.

Stop Estradiol Valerate and Estradiol Valerate/Dienogest if there is unexplained loss of vision, proptosis, diplopia, papilledema, or retinal vascular lesions. Evaluate for retinal vein thrombosis immediately. [See Adverse Reactions (6).]

5.2 Carcinoma of the Breasts and Reproductive Organs

Women who currently have or have had breast cancer should not use Estradiol Valerate and Estradiol Valerate/Dienogest because breast cancer is a hormonally-sensitive tumor.

There is substantial evidence that COCs do not increase the incidence of breast cancer. Although some past studies have suggested that COCs might increase the incidence of breast cancer, more recent studies have not confirmed such findings.

Some studies suggest that COCs are associated with an increase in the risk of cervical cancer or intraepithelial neoplasia. However, there is controversy about the extent to which these findings may be due to differences in sexual behavior and other factors.

Endometrial biopsies performed in a subset of subjects in a Phase 3 Estradiol Valerate and Estradiol Valerate/Dienogest clinical trial did not reveal any unexpected or concerning findings for subjects taking COCs. [See Adverse Reactions (6.1).]

5.3 Liver Disease

Discontinue Estradiol Valerate and Estradiol Valerate/Dienogest if jaundice develops. Steroid hormones may be poorly metabolized in patients with impaired liver function. Acute or chronic disturbances of liver function may necessitate the discontinuation of COC use until markers of liver function return to normal and COC causation has been excluded.

Hepatic adenomas are associated with COC use. An estimate of the attributable risk is 3.3 cases/100,000 COC users. Rupture of hepatic adenomas may cause death through intra-abdominal hemorrhage.

Studies have shown an increased risk of developing hepatocellular carcinoma in long-term (> 8 years) COC users. However, the attributable risk of liver cancers in COC users is less than one case per million users.

Oral contraceptive-related cholestasis may occur in women with a history of pregnancy-related cholestasis. Women with a history of COC-related cholestasis may have the condition recur with subsequent COC use.

5.4 High Blood Pressure

For women with well-controlled hypertension, monitor blood pressure and stop Estradiol Valerate and Estradiol Valerate/Dienogest if blood pressure rises significantly. Women with uncontrolled hypertension or hypertension with vascular disease should not use COCs.

An increase in blood pressure has been reported in women taking COCs, and this increase is more likely in older women and with extended duration of use. The incidence of hypertension increases with increasing concentration of progestin.

5.5 Gallbladder Disease

Studies suggest a small increased relative risk of developing gallbladder disease among COC users.

5.6 Carbohydrate and Lipid Metabolic Effects

Carefully monitor prediabetic and diabetic women who are taking Estradiol Valerate and Estradiol Valerate/Dienogest. COCs may decrease glucose tolerance in a dose-related fashion.

Consider alternative contraception for women with uncontrolled dyslipidemia. A small proportion of women will have adverse lipid changes while on COCs.

Women with hypertriglyceridemia, or a family history thereof, may be at an increased risk of pancreatitis when using COCs.

5.7 Headache

If a woman taking Estradiol Valerate and Estradiol Valerate/Dienogest develops new headaches that are recurrent, persistent, or severe, evaluate the cause and discontinue Estradiol Valerate and Estradiol Valerate/Dienogest if indicated.

An increase in frequency or severity of migraine during COC use (which may be prodromal of a cerebrovascular event) may be a reason for immediate discontinuation of the COC.

5.8 Bleeding Irregularities

Breakthrough bleeding and spotting sometimes occur in patients on COCs, especially during the first three months of use. If bleeding persists or occurs after previously regular cycles, check for causes such as pregnancy or malignancy. If pathology and pregnancy are excluded, bleeding irregularities may resolve over time or with a change to a different COC.

Women who are not pregnant and use Estradiol Valerate and Estradiol Valerate/Dienogest, may experience amenorrhea. Based on patient diaries, amenorrhea occurs in approximately 16% of cycles in women using Estradiol Valerate and Estradiol Valerate/Dienogest. Pregnancy should be ruled out in the event of amenorrhea occurring in two or more consecutive cycles. Some women may encounter amenorrhea or oligomenorrhea after stopping COCs, especially when such a condition was pre-existent.

Based on patient diaries from three clinical trials evaluating the safety and efficacy of Estradiol Valerate and Estradiol Valerate/Dienogest for contraception, 10-23% of women experienced intracyclic bleeding per cycle.

5.9 COC Use Before or During Early Pregnancy

Extensive epidemiological studies have revealed no increased risk of birth defects in women who have used oral contraceptives prior to pregnancy. Studies also do not suggest a teratogenic effect, particularly in so far as cardiac anomalies and limb-reduction defects are concerned, when taken inadvertently during early pregnancy. Oral contraceptive use should be discontinued if pregnancy is confirmed.

The administration of oral contraceptives to induce withdrawal bleeding should not be used as a test for pregnancy [see Use in Specific Populations (8.1)].

5.10 Depression

Women with a history of depression should be carefully observed and Estradiol Valerate and Estradiol Valerate/Dienogest discontinued if depression recurs to a serious degree.

5.11 Interference with Laboratory Tests

The use of COCs may change the results of some laboratory tests, such as coagulation factors, lipids, glucose tolerance, and binding proteins. Women on thyroid hormone replacement therapy may need increased doses of thyroid hormone because serum concentrations of thyroid-binding globulin increase with use of COCs [see Drug Interactions (7.2)].

5.12 Monitoring

A woman who is taking COCs should have a yearly visit with her healthcare provider for a blood pressure check and for other indicated healthcare.

5.13 Drug Interactions

Women who take medications that are strong cytochrome P450 3A4 (CYP3A4) inducers (for example, carbamazepine, phenytoin, rifampicin, and St. John’s wort) should not choose Estradiol Valerate and Estradiol Valerate/Dienogest as their oral contraceptive while using these inducers and for at least 28 days after discontinuation of these inducers due to the possibility of decreased contraceptive efficacy. [See Drug Interactions (7.1) and Clinical Pharmacology (12.3).]

5.14 Other Conditions

In women with hereditary angioedema, exogenous estrogens may induce or exacerbate symptoms of angioedema. Chloasma may occasionally occur, especially in women with a history of chloasma gravidarum. Women with a tendency to chloasma should avoid exposure to the sun or ultraviolet radiation while taking COCs.

6 ADVERSE REACTIONS

The following serious adverse reactions with the use of COCs are discussed elsewhere in the labeling:

- Serious cardiovascular events and stroke [see Boxed Warning and Warnings and Precautions (5.1)]
- Vascular events [see Warnings and Precautions (5.1)]
- Liver disease [see Warnings and Precautions (5.3)]

Adverse reactions commonly reported by COC users are:

- Irregular uterine bleeding
- Nausea
- Breast tenderness
- Headache

6.1 Clinical Trials Experience

Because clinical trials are conducted under widely varying conditions, adverse reaction rates observed in the clinical trials of a drug cannot be directly compared to rates in the clinical trials of another drug and may not reflect the rates observed in practice.

Contraception and Heavy Menstrual Bleeding Studies

A total of 2,131 women, 18 to 54 years of age, who took at least one dose of Estradiol Valerate and Estradiol Valerate/Dienogest were enrolled in four clinical phase 3 trials. A total of 1,867 subjects were included in two clinical phase 3 studies with a treatment duration up to 28 cycles with Estradiol Valerate and Estradiol Valerate/Dienogest as an oral contraceptive and 264 subjects in the two phase 3 clinical trials with a treatment duration of 7 cycles evaluating Estradiol Valerate and Estradiol Valerate/Dienogest in the treatment of heavy, prolonged, and/or frequent menstrual bleeding in women without organic pathology. [See Clinical Studies (14.1, 14.2.)]

Adverse Reactions Leading to Study Discontinuation: 11.4% of the women discontinued from the clinical trials due to an adverse reaction; the most frequent adverse reactions leading to discontinuation were menstrual disorder (metrorrhagia, menorrhagia, menstruation irregular, genital hemorrhage, vaginal hemorrhage, dysfunctional uterine bleeding) (2.3%); mood changes (depression, mood swings, mood altered, depressed mood, dysthymic disorder, crying) (1.2%); acne (1.1%), headache (including migraines) (1.1%), and weight increased (0.7 %).

Common Adverse Reactions (≥ 2%): headache (including migraines) (12.7%), breast pain, discomfort or tenderness (7.0%), menstrual disorders (metrorrhagia, menstruation irregular, menorrhagia, vaginal hemorrhage, dysfunctional uterine bleeding, genital hemorrhage, abnormal withdrawal bleeding, uterine hemorrhage) (6.9%), nausea or vomiting (6.0%), acne (3.9%), mood changes (depression, mood swings, depressed mood, mood altered, affect lability, dysthymic disorder, crying) (3.0%) and increased weight (2.9%).

Serious Adverse Reactions: myocardial infarction (2 cases), ruptured ovarian cyst (2 cases), deep vein thrombosis, focal nodular hyperplasia of the liver, uterine leiomyoma, acute cholecystitis, and chronic acalculous cholecystitis.

6.2 Postmarketing Experience

The following adverse reactions have been identified during post-approval use of Estradiol Valerate and Estradiol Valerate/Dienogest. Because these reactions are reported voluntarily from a population of uncertain size, it is not always possible to reliably estimate their frequency or establish a causal relationship to drug exposure.

Vascular disorders: Venous and arterial thromboembolic events (including pulmonary emboli, deep vein thrombosis, cerebral thrombosis, myocardial infarction and stroke), hypertension

Hepatobiliary disorders: Gallbladder disease, hepatitis

Immune system disorders: Hypersensitivity

Metabolism and nutrition disorders: Fluid retention, hypertriglyceridemia

Nervous system disorders: Dizziness

Skin and subcutaneous tissue disorders: Chloasma, angioedema, erythema nodosum, erythema multiforme

Gastrointestinal disorders: Gastrointestinal symptoms (for example, abdominal pain)

Infections and infestations: Vulvovaginal candidiasis

7 DRUG INTERACTIONS

Consult the labeling of all concurrently-used drugs to obtain further information about interactions with hormonal contraceptives or the potential for enzyme alterations.

7.1 Effects of Other Drugs on Combined Oral Contraceptives

Interactions between oral contraceptives and other drugs may lead to breakthrough bleeding and/or contraceptive failure. The following interactions have been reported in the literature for COCs in general or were studied in clinical trials with Estradiol Valerate and Estradiol Valerate/Dienogest.

CYP3A4 Inducers: Drugs or herbal products that induce certain enzymes, including CYP3A4, may decrease the effectiveness of COCs or increase breakthrough bleeding. Some drugs or herbal products that may decrease the effectiveness of hormonal contraceptives include barbiturates, bosentan, felbamate, griseofulvin, oxcarbazepine, and topiramate. Counsel women to use an alternative method of contraception or a back-up method when moderate or weak enzyme inducers are used with COCs, and to continue back-up contraception for 28 days after discontinuing the enzyme inducer to ensure contraceptive reliability.

Dienogest is a substrate of CYP3A4. Women who take medications that are strong CYP3A4 inducers (for example, carbamazepine, phenytoin, rifampicin, and St. John’s wort) should not choose Estradiol Valerate and Estradiol Valerate/Dienogest as their oral contraceptive while using these inducers and for at least 28 days after discontinuation of these inducers due to the possibility of decreased contraceptive efficacy.

The effect of the CYP3A4 inducer rifampicin was studied in healthy postmenopausal women. Co-administration of rifampicin with estradiol valerate/dienogest tablets led to a 52 % and 83% decrease in the mean Cmax and AUC (0–24hr), respectively, for dienogest and a 25% and 44% decrease in Cmax and AUC (0–24hr), respectively, for estradiol at steady state.

Strong CYP3A4 Inhibitors: Strong CYP3A4 inhibitors such as ketoconazole increased hormone serum concentrations. In a study investigating the effect of ketoconazole on dienogest and estradiol pharmacokinetics, co-administration with the strong CYP3A4 inhibitor ketoconazole resulted in a 186% increase of AUC (0–24hr) at steady state for dienogest and a 57% increase for estradiol. There was also a 94% and 65% increase of Cmax at steady state for dienogest and estradiol when co-administered with ketoconazole.

Moderate CYP3A4 Inhibitors: The AUC (0–24hr) of dienogest and estradiol at steady state were increased by 62% and 33%, respectively, when co-administered with a moderate CYP3A4 inhibitor, erythromycin. There was also a 33% and 51% increase of Cmax at steady state for dienogest and estradiol, respectively, when co-administered with erythromycin.

Other known CYP3A4 inhibitors like azole antifungals, cimetidine, verapamil, macrolides, diltiazem, antidepressants, and grapefruit juice may increase plasma concentrations of dienogest.

Human Immunodeficiency Virus (HIV)/Hepatitis C Virus (HCV) Protease Inhibitors and Non-Nucleoside Reverse Transcriptase Inhibitors: Significant changes (increase and decrease) in plasma concentrations of estrogen and progestin have been noted in some cases of co-administration of HIV/HCV protease inhibitors or with non-nucleoside reverse transcriptase inhibitors.

Antibiotics: There have been reports of pregnancy while taking hormonal contraceptives and antibiotics, but clinical pharmacokinetic studies have not shown consistent effects of antibiotics on plasma concentrations of synthetic steroids.

7.2 Effects of Combined Oral Contraceptives on Other Drugs

COCs containing ethinyl estradiol may inhibit the metabolism of other compounds. COCs have been shown to significantly decrease plasma concentrations of lamotrigine, likely due to induction of lamotrigine glucuronidation. This may reduce seizure control; therefore, dosage adjustments of lamotrigine may be necessary. Consult the labeling of the concurrently-used drug to obtain further information about interactions with COCs or the potential for enzyme alterations.

In vitro studies with human CYP enzymes did not indicate an inhibitory potential of dienogest at clinically relevant concentrations.

Women on thyroid hormone replacement therapy may need increased doses of thyroid hormone because serum concentrations of thyroid-binding globulin increase with use of COCs.

7.3 Interference with Laboratory Tests

The use of contraceptive steroids may influence the results of certain laboratory tests, such as coagulation factors, lipids, glucose tolerance, and binding proteins [see Warnings and Precautions (5.11) and Drug Interactions (7.2)].

8 USE IN SPECIFIC POPULATIONS

8.1 Pregnancy

There is little or no increased risk of birth defects in women who inadvertently use COCs during early pregnancy. Epidemiologic studies and meta-analyses have not found an increased risk of genital or non-genital birth defects (including cardiac anomalies and limb-reduction defects) following exposure to low dose COCs prior to conception or during early pregnancy.

The administration of COCs to induce withdrawal bleeding should not be used as a test for pregnancy. COCs should not be used during pregnancy to treat threatened or habitual abortion.

Women who do not breastfeed may start COCs no earlier than four weeks postpartum.

8.3 Nursing Mothers

When possible, advise the nursing mother to use other forms of contraception until she has weaned her child. Estrogen-containing COCs can reduce milk production in breastfeeding mothers. This is less likely to occur once breastfeeding is well-established; however, it can occur at any time in some women. Small amounts of oral contraceptive steroids and/or metabolites are present in breast milk.

8.4 Pediatric Use

Safety and efficacy of Estradiol Valerate and Estradiol Valerate/Dienogest have been established in women of reproductive age. Efficacy is expected to be the same for postpubertal adolescents under the age of 18 and for users 18 years and older. Use of this product before menarche is not indicated.

8.5 Geriatric Use

Estradiol Valerate and Estradiol Valerate/Dienogest has not been studied in postmenopausal women and is not indicated in this population.

8.6 Patients with Renal Impairment

The pharmacokinetics of Estradiol Valerate and Estradiol Valerate/Dienogest has not been studied in subjects with renal impairment, but an effect requiring dose adjustment is unlikely to be present [see Clinical Pharmacology (12.3)].

8.7 Patients with Hepatic Impairment

The pharmacokinetics of Estradiol Valerate and Estradiol Valerate/Dienogest has not been studied in subjects with hepatic impairment. Steroid hormones may be poorly metabolized in patients with impaired liver function. Acute or chronic disturbances of liver function may necessitate the discontinuation of COC use until markers of liver function return to normal. [See Contraindications (4) and Warnings and Precautions (5.3).)]

8.8 Body Mass Index

The safety and efficacy of Estradiol Valerate and Estradiol Valerate/Dienogest in women with a BMI of > 30 kg/m^2 has not been evaluated.

10 OVERDOSAGE

There have been no reports of serious ill effects from overdose, including ingestion by children. Overdosage may cause withdrawal bleeding in females and nausea.

11 DESCRIPTION

Estradiol Valerate and Estradiol Valerate/Dienogest tablets provide an oral contraceptive regimen consisting of 26 active film-coated tablets that contain the active ingredients specified for each tablet below, followed by two inert film-coated tablets:

- 2 dark yellow tablets each containing 3 mg estradiol valerate
- 5 medium red tablets each containing 2 mg estradiol valerate and 2 mg dienogest
- 17 light yellow tablets each containing 2 mg estradiol valerate and 3 mg dienogest
- 2 dark red tablets each containing 1 mg estradiol valerate
- 2 white tablets (inert)

Estradiol Valerate and Estradiol Valerate/Dienogest also contains the excipients lactose monohydrate, maize starch, maize starch pre-gelatinized, povidone 25, magnesium stearate, hypromellose, macrogol 6000, talc, titanium dioxide, and ferric oxide pigment, yellow, or ferric oxide pigment, red.

The empirical formula of estradiol valerate is C23 H32 O3 and the chemical structure is:

Estradiol Valerate

Estradiol Valerate

The chemical name of estradiol valerate is Estra-1,3,5(10)-triene-3,17-diol(17ß)-,17-pentanoate.

The empirical formula of dienogest is C20 H25 NO2 and the chemical structure is:

Dienogest

Dienogest

The chemical name of dienogest is (17α)-17-Hydroxy-3-oxo-19-norpregna-4,9-diene-21-nitrile.

12 CLINICAL PHARMACOLOGY

12.1 Mechanism of Action

COCs lower the risk of becoming pregnant primarily by suppressing ovulation. Other possible mechanisms may include cervical mucus changes that inhibit sperm penetration and endometrial changes that reduce the likelihood of implantation.

12.2 Pharmacodynamics

The estrogen in Estradiol Valerate and Estradiol Valerate/Dienogest is estradiol valerate, a synthetic prodrug of 17ß-estradiol.

The progestin in Estradiol Valerate and Estradiol Valerate/Dienogest is dienogest (DNG). DNG displays properties of 19-nortestosterone derivatives as well as properties associated with progesterone derivatives. [See Nonclinical Toxicology (13.2).]

Cardiac Electrophysiology

The effect of Estradiol Valerate and Estradiol Valerate/Dienogest on QT prolongation was evaluated in a randomized, double-blind, positive (moxifloxacin 400 mg) and negative (placebo) controlled crossover study in healthy subjects. A total of 53 subjects were administered Estradiol Valerate and Estradiol Valerate/Dienogest (containing 3 mg dienogest and 2 mg estradiol valerate), dienogest 10 mg, and placebo as once daily doses for 4 days, and moxifloxacin 400 mg as a single oral dose. The upper bound of the 90% confidence interval for the largest placebo-adjusted, baseline-corrected QTc based on Fridericia’s correction method (QTcF) was below 10 msec, the threshold for regulatory concern.

12.3 Pharmacokinetics

Absorption

After oral administration of estradiol valerate, cleavage to 17β-estradiol and valeric acid takes place during absorption by the intestinal mucosa or in the course of the first liver passage. This gives rise to estradiol and its metabolites, estrone and other metabolites. Maximum serum estradiol concentrations of 73.3 pg/mL are reached at a median of approximately 6 hours (range: 1.5–12 hours) and the area under the estradiol concentration curve [AUC(0–24hr)] was 1301 pg·hr/mL after single ingestion of a tablet containing 3 mg estradiol valerate under fasted condition on Day 1 of the 28-day sequential regimen.

Bioavailability of dienogest is about 91%. Maximum serum dienogest concentrations of 91.7 ng/mL are reached at a median of approximately 1 hour (range: 0.5–1.5 hour) and the area under the dienogest concentration curve [AUC(0–24hr)] was 964 ng/mL after single oral administration of Estradiol Valerate and Estradiol Valerate/Dienogest tablet containing 2 mg estradiol valerate/3 mg dienogest under fasted condition. The pharmacokinetics of dienogest are dose-proportional within the dose range of 1–8 mg. Steady state is reached after 4 days of the same dosage of 2 mg dienogest. The mean accumulation ratio for AUC (0–24hr) is approximately 1.24.

The mean plasma pharmacokinetic parameters at steady state following repeated oral doses of a 2 mg estradiol valerate/3 mg dienogest combination tablet in fertile women under fasted condition are reported in Table 1.

Table 1 Arithmetic Mean (SD) Serum Pharmacokinetic Parameters at Steady-state (on Day 24) following Repeated Oral Doses of 2 mg EV/3 mg DNG on Days 8-24 of the 28 day Regimen in Fertile Women under Fasted Condition (N=15)
Parameter | Dienogest | Estradiol | Estrone
Cmax [Cmax = Maximum serum concentration] | 85.2 (19.7) ng/ml | 70.5 (25.9) pg/ml | 483 (198) pg/ml
Tmax [Tmax = Time to reach maximum concentration] (hr) [Median (range) for Tmax] | 1.5 (1–2) | 3 (1.5–12) | 4 (3–12)
AUC [AUC(0-24hr) = Area under the concentration-time curve from 0 hr data point up to 48 hr post-administration] (0–24hr) | 828 (187) ng·hr/ml | 1323 (480) pg·hr/ml | 7562 (3403) pg·hr/ml
t½ (hr) | 12.3 (1.4) | NA [NA: Data not available] | NA

Food Effect

Concomitant food intake in women resulted in a 28% decrease for dienogest Cmax and 23% increase of estradiol Cmax while the exposure (AUC) of both dienogest and estradiol did not change.

Distribution

In serum, 38% of estradiol is bound to sex hormone-binding globulin (SHBG), 60% to albumin and 2–3% circulates in free form. An apparent volume of distribution of approximately 1.2 L/kg was determined after intravenous (IV) administration.

A relatively high fraction (10%) of circulating dienogest is present in the free form, with approximately 90% being bound non-specifically to albumin. Dienogest does not bind to SHBG and corticosteroid-binding globulin (CBG). The volume of distribution at steady state (Vd,ss) of dienogest is 46 L after the IV administration of 85 mcg ^3H-dienogest.

Metabolism

After oral administration of estradiol valerate, approximately 3% of the dose is directly bioavailable as estradiol. Estradiol undergoes an extensive first-pass effect and a considerable part of the dose administered is already metabolized in the gastrointestinal mucosa. The CYP 3A family is known to play the most important role in human estradiol metabolism. Together with the pre-systemic metabolism in the liver, about 95% of the orally administered dose becomes metabolized before entering the systemic circulation. The main metabolites are estrone and its sulfate or glucuronide conjugates.

Dienogest is extensively metabolized by the known pathways of steroid metabolism (hydroxylation, conjugation), with the formation of endocrinologically mostly inactive metabolites. CYP3A4 was identified as a predominant enzyme catalyzing the metabolism of dienogest.

Excretion

Estradiol and its metabolites are mainly excreted in urine, with about 10% being excreted in the feces. The terminal half-life of estradiol is approximately 14 hours.

Dienogest is mainly excreted renally in the form of metabolites and unchanged dienogest is the dominating fraction in plasma. The terminal half-life of dienogest is approximately 11 hours.

Use in Specific Populations

Pediatric Use: Safety and efficacy of Estradiol Valerate and Estradiol Valerate/Dienogest has been established in women of reproductive age. Efficacy is expected to be the same for postpubertal adolescents under the age of 18 and for users 18 years and older. Use of this product before menarche is not indicated.

Geriatric Use: Estradiol Valerate and Estradiol Valerate/Dienogest has not been studied in postmenopausal women and is not indicated in this population.

Renal Impairment: The pharmacokinetics of Estradiol Valerate and Estradiol Valerate/Dienogest has not been studied in subjects with renal impairment.

Hepatic Impairment: The pharmacokinetics of Estradiol Valerate and Estradiol Valerate/Dienogest has not been studied in subjects with hepatic impairment.Steroid hormones may be poorly metabolized in patients with impaired liver function. Acute or chronic disturbances of liver function may necessitate the discontinuation of COC use until markers of liver function return to normal. [See Contraindications (4) and Warnings and Precautions (5.3).]

Body Mass Index: The efficacy of Estradiol Valerate and Estradiol Valerate/Dienogest in women with a BMI of > 30 kg/m^2 has not been evaluated.

Drug Interactions

Consult the labeling of all concurrently used drugs to obtain further information about interactions with oral contraceptives or the potential for enzyme alterations.

Effects of Other Drugs on Combined Oral Contraceptives

CYP3A4 Inducers: Drugs or herbal products that induce certain enzymes, including CYP3A4, may decrease the effectiveness of COCs or increase breakthrough bleeding. Some drugs or herbal products that may decrease the effectiveness of hormonal contraceptives include barbiturates, bosentan, felbamate, griseofulvin, oxcarbazepine, and topiramate. Counsel women to use an alternative method of contraception or a back-up method when moderate or weak enzyme inducers are used with COCs, and to continue back-up contraception for 28 days after discontinuing the enzyme inducer to ensure contraceptive reliability.

Dienogest is a substrate of CYP3A4. Women who take medications that are strong CYP3A4 inducers (for example, carbamazepine, phenytoin, rifampicin, and St. John’s wort) should not choose Estradiol Valerate and Estradiol Valerate/Dienogest as their oral contraceptive while using these inducers and for at least 28 days after discontinuation of these inducers due to the possibility of decreased contraceptive efficacy.

The effect of the CYP3A4 inducer rifampicin was studied in an open-label, non-randomized, single center study in 16 healthy postmenopausal women. All volunteers received a treatment regimen of 2 mg estradiol valerate and 3 mg dienogest combination tablets, dosed once daily over 17 days, and of rifampicin, which was administered once daily in an oral dose of 600 mg on Days 12 to 16. 24–hr pharmacokinetics of estradiol and dienogest on Days 11 and 17 were compared. Co-administration of rifampicin with estradiol valerate/dienogest tablets led to a 52 % and 83% decrease in the mean Cmax and AUC(0–24hr), respectively, for dienogest and a 25% and 44% decrease in Cmax and AUC(0–24hr), respectively, for estradiol at steady state.

Strong CYP3A4 Inhibitors: Strong CYP3A4 inhibitors such as ketoconazole increase hormone serum concentrations. The effect of a strong CYP3A4 inhibitor, ketoconazole, on dienogest and estradiol pharmacokinetics was studied in an open-label, two parallel-groups, one-sequence, one-way crossover study in healthy postmenopausal Caucasian women. One tablet of 2 mg estradiol valerate and 3 mg dienogest was administered orally once a day for 14 days. Twelve volunteers received an oral dose of 400 mg ketoconazole (that is, 2 tablets containing 200 mg ketoconazole) once daily for 7 days (Days 8–14). Twenty-four hour pharmacokinetics of estradiol and dienogest on Days 7 and 14 were compared. Co-administration with the strong inhibitor ketoconazole resulted in a 186% and 57% increase of AUC (0–24hr) at steady state for dienogest and estradiol. There was also a 94% and 65% increase of Cmax at steady state for dienogest and estradiol when co-administered with ketoconazole.

Moderate CYP3A4 Inhibitors: Moderate CYP3A4 inhibitors such as erythromycin increase hormone serum concentrations. The effect of a moderate CYP3A4 inhibitor, erythromycin on dienogest and estradiol pharmacokinetics was studied in an open-label, two parallel-groups, one-sequence, one-way crossover study in healthy postmenopausal Caucasian women. One tablet of 2 mg estradiol valerate and 3 mg dienogest was administered orally once a day for 14 days. Twelve volunteers received an oral dose of 500 mg erythromycin three times a day for 7 days (Days 8–14). Twenty-four hour pharmacokinetics of estradiol and dienogest on Days 7 and 14 were compared. When co-administered with the moderate inhibitor erythromycin, the AUC (0–24hr) of dienogest and estradiol at steady state were increased by 62% and 33%, respectively. There was also a 33% and 51% increase of Cmax at steady state for dienogest and estradiol when co-administered with erythromycin.

Other known CYP3A4 inhibitors such as azole antifungals, cimetidine, verapamil, macrolides, diltiazem, antidepressants, and grapefruit juice may increase plasma concentrations of dienogest and estradiol.

HIV/HCV Protease Inhibitors and non-nucleoside reverse transcriptase inhibitors: Significant changes (increase or decrease) in the plasma concentrations of the estrogen and progestin have been noted in some cases of co-administration of HIV/HCV protease inhibitors or with non-nucleoside reverse transcriptase inhibitors.

Antibiotics: There have been reports of pregnancy while taking hormonal contraceptives and antibiotics, but clinical pharmacokinetic studies have not shown consistent effects of antibiotics on plasma concentrations of synthetic steroids.

Effects of Combined Oral Contraceptives on Other Drugs

COCs containing ethinyl estradiol may inhibit the metabolism of other compounds. COCs have been shown to significantly decrease plasma concentrations of lamotrigine, likely due to induction of lamotrigine glucuronidation. This may reduce seizure control; therefore, dosage adjustments of lamotrigine may be necessary. Consult the labeling of the concurrently-used drug to obtain further information about interactions with COCs or the potential for enzyme alterations.

In vitro studies with human CYP enzymes did not indicate an inhibitory potential of dienogest at clinically relevant concentrations.

Women on thyroid hormone replacement therapy may need increased doses of thyroid hormone because serum concentration of thyroid-binding globulin increases with use of COCs.

13 NONCLINICAL TOXICOLOGY

13.1 Carcinogenesis, Mutagenesis, Impairment of Fertility

In a 24 month carcinogenicity study in mice dosed orally with dienogest by gavage with doses of 5, 15 and 50 mg/kg/day (males) and 10, 30 and 100 mg/kg/day (females), the systemic exposures in the females were 1.1, 3.5, and 10.6 times the exposure (AUC of dienogest) of women taking a 3 mg dose. A statistically significantly higher incidence of stromal polyps of the uterus was observed in females given 100 mg/kg. In a similar study in rats given 1, 3, and 10 mg/kg for 104 weeks, 0.2, 1.4, and 6.1 times the exposure of women taking a 3 mg dose, there were no statistically significant drug-related neoplasms.

Dienogest was not mutagenic in in vitro reverse mutation tests in bacteria, in chromosome aberration tests in human peripheral lymphocytes, mouse lymphoma cells, and Chinese hamster lung cells, and tests of unscheduled DNA synthesis (UDS) in rat and human liver cells. Dienogest was also negative in an in vivo mouse micronucleus test, a rat liver initiation-promotion model, and an in vitro/in vivo UDS test in female rats.

13.2 Animal Toxicology and/or Pharmacology

Nonclinical studies in animals and in vitro, have shown that besides progestogenic activities, DNG is devoid of estrogenic, androgenic, glucocorticoid and mineralocorticoid activities.

14 CLINICAL STUDIES

14.1 Oral Contraceptive Clinical Trials

The study conducted in North America (U.S. and Canada) was a multicenter, open-label, single-arm, unintended pregnancy study. There were 490 healthy subjects between 18 and 35 years of age (mean age: 25.1 years) who were treated for up to 28 cycles of 28 days each. The racial demographic of enrolled women was: Caucasian (76%), Hispanic (13%), African-American (7%), Asian (3%), and Other (1%). The weight range for treated women was 40 to 100 kg (mean weight: 62.5 kg) and the BMI range was 14 to 30 kg/m^2 (mean BMI: 23.3 kg/m^2). Of treated women, 15% discontinued the study treatment due to an adverse event, 13% were lost to follow up, 10% withdrew their consent, 8% discontinued due to other reason, 1% discontinued due to protocol deviation, and 1% discontinued due to pregnancy.

The study conducted in Europe (Germany, Austria and Spain) was a multicenter, open-label, single-arm contraceptive reliability study. There were 1,377 healthy subjects between 18 and 50 years of age (mean age: 30.3 years) who were treated for 20 cycles of 28 days each. The racial demographic of enrolled women was predominantly Caucasian (99.2%). The weight range for treated women was 38 to 98 kg (mean weight: 63.8 kg) and the BMI range was 15 to 31.8 kg/m^2 (mean BMI: 22.8 kg/m^2). Of treated women, 10% discontinued the study treatment due to an adverse event, 5% discontinued due to other reason, 2% were lost to follow up, 2% discontinued due to protocol deviation, 2% withdrew their consent, and 1% discontinued due to pregnancy.

The Pearl Index (PI) was the primary efficacy endpoint used to assess contraceptive reliability and was assessed in each of the two studies, assuming all subjects were at risk of pregnancy in all medication cycles unless back-up contraception was documented. The PI is based on pregnancies that occurred after the onset of treatment and within 7 days after the last pill intake. Cycles in which conception did not occur, but which included the use of back-up contraception, were not included in the calculation of the PI. The PI also includes patients who did not take the drug correctly. The estimated PI for the North American study is 1.64 and the estimated PI for the European study is 1.04. The Kaplan-Meier method was also used to calculate the contraceptive failure rate.

The summary of the Pearl Indexes and cumulative contraceptive failure rates are provided in Table 2:

Table 2 Summary of the Pearl Indexes and the Cumulative Contraceptive Failure Rates
Study | Age Group | Relative Treatment Exposure Cycles [Total treatment exposure time without back-up contraception] | Number of Pregnancies within 13 Cycles and 7 Days after Last Treatment | Pearl Index | Upper Limit of 95% CI | Contraceptive Failure Rate at the End of First Year
North America | 18–35 | 3,969 | 5 | 1.64 | 3.82 | 0.016
Europe | 18–35 | 11,275 | 9 | 1.04 | 1.97 | 0.010

14.2 Heavy Menstrual Bleeding Clinical Trials

The efficacy and safety of Estradiol Valerate and Estradiol Valerate/Dienogest were evaluated in two multi-regional, multicenter, double-blind, randomized, placebo-controlled clinical trials. Study 308960 was performed in the United States and Canada and Study 308961 was performed in Australia and 9 European countries. The studies were identical in design. The studies enrolled women, 18 years of age or older, with a diagnosis of dysfunctional uterine bleeding characterized as heavy, prolonged and/or frequent bleeding without organic pathology. Heavy menstrual bleeding (HMB) was defined as menstrual blood loss of 80 mL or more in at least 2 bleeding episodes. The diagnosis of HMB was documented through the collection of used sanitary protection (pads and tampons) to quantify blood loss assessed by the alkaline hematin method. Overall, about 85% of the subjects qualified for the study because they had heavy menstrual bleeding symptoms.

A total of 421 women with a mean age of 38.2 and a mean BMI of 25.5 were randomized to the two clinical studies, for a total of 269 women in the Estradiol Valerate and Estradiol Valerate/Dienogest group and 152 women in the placebo group, and treated for seven 28-day cycles. Approximately 81% were Caucasian, 13% were Black, and 6% were Hispanic or Asian or Other.

The primary efficacy variable was the proportion of subjects who were completely relieved of symptoms, which was defined by the number of subjects with the absence of any dysfunctional bleeding symptom and who met up to 8 strictly defined criteria for success during the 90-day efficacy assessment phase. In Study 308960, the proportion of the intent-to-treat subjects with complete symptom relief was 29.2% in the Estradiol Valerate and Estradiol Valerate/Dienogest group compared to 2.9% in the placebo group. In Study 308961, the proportion of the intent-to-treat subjects with complete symptom relief was 29.5% in the Estradiol Valerate and Estradiol Valerate/Dienogest group compared to 1.2% in the placebo group.

In both studies, Natazia was effective in treating the symptoms of HMB in the subset of women who entered the study with symptoms specific to HMB. Among patients with HMB, menstrual blood loss (MBL) was statistically significantly reduced in the group treated with Natazia compared with placebo (p<0.0001 for both studies). Evaluating data based on 28-day cycles, the median menstrual blood volume at Cycle 7 was reduced from the baseline median by 90% in one trial and 87% in the other. For women treated with placebo, the median menstrual blood volume at Cycle 7 was reduced from the baseline median by 14% and 32% in the two trials, respectively. Figures 1 and 2 display the MBL volume by cycle and by study.

Figure 1 Median Menstrual Blood Loss Volume by Cycle (Study 308960)
Figure 2 Median Menstrual Blood Loss Volume by Cycle (Study 308961)

16 HOW SUPPLIED/STORAGE AND HANDLING

16.1 How Supplied

Estradiol Valerate and Estradiol Valerate/Dienogest tablets are available in packages of three blister packs (NDC 50419-409-03).

The active and inert film-coated tablets are rounded with biconvex faces, one side is embossed with a regular hexagon shape with the letters DD or DJ or DH or DN or DT.

Each blister pack (28 film-coated tablets) contains in the following order:

- 2 round biconvex dark yellow film-coated tablets with embossed “DD” in a regular hexagon on one side each containing 3 mg estradiol valerate
- 5 round biconvex medium red film-coated tablets with embossed “DJ” in a regular hexagon on one side each containing 2 mg estradiol valerate and 2 mg dienogest
- 17 round biconvex light yellow film-coated tablets with embossed “DH” in a regular hexagon on one side each containing 2 mg estradiol valerate and 3 mg dienogest
- 2 round biconvex dark red film-coated tablets with embossed “DN” in a regular hexagon on one side each containing 1 mg estradiol valerate
- 2 white round biconvex white film-coated tablets with embossed “DT” in a regular hexagon on one side (inert)

16.2 Storage

Store at 25º C (77º F); excursions permitted to 15–30oC (59–86oF) [see USP Controlled Room Temperature].

17 PATIENT COUNSELING INFORMATION

See “FDA-approved patient labeling (Patient Information).”

- Counsel patients that cigarette smoking increases the risk of serious cardiovascular events from COC use, and that women who are over 35 years old and smoke should not use COCs.
- Counsel patients that the increased risk of VTE compared to non-users of COCs is greatest after initially starting a COC or restarting (following a 4 week or greater pill-free interval) the same or a different COC.
- Counsel patients that Estradiol Valerate and Estradiol Valerate/Dienogest does not protect against HIV infection (AIDS) and other sexually transmitted diseases.
- Counsel patients on Warnings and Precautions associated with COCs.
- Inform patients that Estradiol Valerate and Estradiol Valerate/Dienogest is not indicated during pregnancy. If pregnancy occurs during treatment with Estradiol Valerate and Estradiol Valerate/Dienogest, instruct the patient to stop further intake.
- Counsel patients to take one tablet daily by mouth at the same time every day in the exact order noted on the blister. Instruct patients what to do in the event pills are missed. See What Should I Do if I Miss any Pills section in FDA-Approved Patient Labeling.
- Counsel women who are taking strong CYP3A4 inducers (for example, carbamazepine, phenytoin, rifampicin, and St. John’s wort) not to choose Estradiol Valerate and Estradiol Valerate/Dienogest as their oral contraceptive due to the possibility of decreased contraceptive efficacy.
- Counsel patients to use a back-up or alternative method of contraception when weak or moderate enzyme inducers are used with Estradiol Valerate and Estradiol Valerate/Dienogest.
- Counsel patients who are breastfeeding or who desire to breastfeed that COCs may reduce breast milk production. This is less likely to occur if breastfeeding is well established.
- Counsel any patient who starts COCs postpartum, and who has not yet had a period, to use an additional method of contraception until she has taken Estradiol Valerate and Estradiol Valerate/Dienogest for 9 consecutive days.
- Counsel patients that amenorrhea may occur. Rule out pregnancy in the event of amenorrhea in two or more consecutive cycles.

FDA-Approved Patient Labeling

Guide for Using Estradiol Valerate and Estradiol Valerate/Dienogest

WARNING TO WOMEN WHO SMOKE

Do not use Estradiol Valerate and Estradiol Valerate/Dienogest if you smoke cigarettes and are over 35 years old. Smoking increases your risk of serious cardiovascular side effects (heart and blood vessel problems) from birth control pills, including death from heart attack, blood clots or stroke. This risk increases with age and the number of cigarettes you smoke.

Birth control pills help to lower the chances of becoming pregnant when taken as directed. They do not protect against HIV infection (AIDS) and other sexually transmitted diseases.

What Is Estradiol Valerate and Estradiol Valerate/Dienogest?

Estradiol Valerate and Estradiol Valerate/Dienogest is a birth control pill. It contains two female hormones, an estrogen called estradiol valerate and a progestin called dienogest. Estradiol valerate is a synthetic estrogen that is converted to estradiol in your body.

Estradiol Valerate and Estradiol Valerate/Dienogest is used to treat heavy menstruation (your monthly period) that is not caused by any diagnosed conditions of the uterus (womb) in women who decide to use an oral contraceptive for birth control. Talk to your healthcare provider to determine if your bleeding is heavier than normal.

How Does Estradiol Valerate and Estradiol Valerate/Dienogest Work?

Birth control pills prevent your ovaries from producing and releasing mature eggs. Estradiol Valerate and Estradiol Valerate/Dienogest decreases menstrual bleeding by thinning the lining of the uterus.

How Well Does Estradiol Valerate and Estradiol Valerate/Dienogest Work For Contraception?

Your chance of getting pregnant depends on how well you follow the directions for taking your birth control pills. The better you follow the directions, the less chance you have of getting pregnant.

Based on the results of two clinical studies, 1 to 2 women out of 100 women may get pregnant during the first year they use Estradiol Valerate and Estradiol Valerate/Dienogest.

The following chart shows the chance of getting pregnant for women who use different methods of birth control. Each box on the chart contains a list of birth control methods that are similar in effectiveness. The most effective methods are at the top of the chart. The box on the bottom of the chart shows the chance of getting pregnant for women who do not use birth control and are trying to get pregnant.

How Well Does Estradiol Valerate and Estradiol Valerate/Dienogest Work For Heavy Menstrual Bleeding?

In two clinical trials in women with heavy menstrual bleeding who were treated with Estradiol Valerate and Estradiol Valerate/Dienogest, their menstrual bleeding was reduced by an average of 90% in one trial and 87% in the other. For women treated with placebo, their menstrual bleeding was reduced by an average of 14% and 32% in the two trials, respectively.

How Do I Take Estradiol Valerate and Estradiol Valerate/Dienogest?

- Take one pill every day at the same time. Take the pills in the order directed on the blister pack.
- Do not skip pills or delay taking your pill by more than 12 hours. If you miss pills (including starting the pack late), you could get pregnant. The more pills you miss, the more likely you are to get pregnant.
- If you have trouble remembering to take Estradiol Valerate and Estradiol Valerate/Dienogest, talk to your healthcare provider about how to make pill-taking easier, or about using another method of birth control.
- You may have spotting or light bleeding when you first take Estradiol Valerate and Estradiol Valerate/Dienogest. Spotting or light bleeding is normal at first.
- You may feel sick to your stomach (nauseous), especially during the first few months that you take Estradiol Valerate and Estradiol Valerate/Dienogest. If you feel sick to your stomach, do not stop taking the pill. The problem will usually go away. If your nausea doesn't go away, call your healthcare provider.
- If you vomit or have diarrhea within 4 hours of taking your pill, follow the instructions for “What Should I Do if I Miss any Pills.”
- Missing pills can also cause spotting or light bleeding, even when you take the missed pills later. On the days you take 2 pills to make up for missed pills, you could also feel a little sick to your stomach.

Before you start taking Estradiol Valerate and Estradiol Valerate/Dienogest

- Decide what time of day you want to take your pill. It is important to take it at the same time every day and in the order as directed on the blister pack.

- Look at your Estradiol Valerate and Estradiol Valerate/Dienogest blister pack. The blister pack has 4 rows of 7 pills each, for a total of 28 pills. Find:
  - where on the pack to start taking your pills
  - in what order to take the pills

Each Estradiol Valerate and Estradiol Valerate/Dienogest blister pack has 28 pills

  - 2 dark yellow pills with hormones, for Days 1 and 2
  - 5 medium red pills with hormones for Days 3–7
  - 17 light yellow pills with hormones for Days 8–24
  - 2 dark red pills with hormones for Days 25 and 26
  - 2 white pills without hormones for Days 27 and 28
- After taking the last white pill (day 28) of the blister pack, start taking the first dark yellow pill from a new blister pack the very next day whether or not you are having your period.
- Be sure to have ready at all times another kind of birth control (such as condoms and spermicides) to use as a back-up in case you miss pills.
- It is not uncommon to miss a period. However, if you miss 2 periods in a row or feel like you may be pregnant, call your healthcare provider. If you are pregnant, you should stop taking Estradiol Valerate and Estradiol Valerate/Dienogest.
When to Start Estradiol Valerate and Estradiol Valerate/Dienogest

If you start taking Estradiol Valerate and Estradiol Valerate/Dienogest and you did not use a hormonal birth control method before:

- Take the first dark yellow pill on the first day (Day 1) of your natural menstrual cycle. The first day of your menstrual cycle is the first day you start spotting or bleeding.
- Use non-hormonal back-up contraception such as a condom and spermicide for the first 9 days that you take Estradiol Valerate and Estradiol Valerate/Dienogest.

If you start taking Estradiol Valerate and Estradiol Valerate/Dienogest and you are switching from a combination hormonal method such as:

  - another pill
  - vaginal ring
  - patch
- Take the first dark yellow pill on the first day of your period. Do not continue taking the pills from your previous birth control pack. If you do not have a period, contact your healthcare provider before you start Estradiol Valerate and Estradiol Valerate/Dienogest.
- If you previously used a vaginal ring or transdermal patch, you should start using Estradiol Valerate and Estradiol Valerate/Dienogest on the day the ring or patch is removed.
- Use a non-hormonal back-up method such as a condom and spermicide for the first 9 days you take Estradiol Valerate and Estradiol Valerate/Dienogest.

If you start taking Estradiol Valerate and Estradiol Valerate/Dienogest and you are switching from a progestin-only method such as a:

  - progestin-only pill
  - implant
  - intrauterine system
  - injection
- Take the first dark yellow pill on the day you would have taken your next progestin-only pill or on the day of removal of your implant or intrauterine system or on the day when you would have had your next injection.
- Use a non-hormonal back-up method such as a condom and spermicide for the first 9 days you take Estradiol Valerate and Estradiol Valerate/Dienogest.

What Should I Do if I Miss any Pills

If you forgot to start a new blister pack, you may already be pregnant. Use back-up contraception (such as condoms and spermicides) anytime you have sex. Call your healthcare provider if you are unsure whether you are pregnant.

- Do not take more than 2 pills in one day. On the days you take 2 pills to make up for missed pills, you may feel a little sick to your stomach (nauseous).
- If you start vomiting or have diarrhea within 4 hours of taking your pill, take another pill of the same color from your extra blister pack.

If you are less than 12 hours late taking your pill

- Take your pill as soon as you remember.
- Take the next pill at the usual time.
- You do not need to use back-up contraception.

If you miss ONE PILL for more than 12 hours

Days 1–17

- Take your missed pill immediately.
- Take your next pill at the usual time (you may have to take two pills that day).
- Use back-up contraception for the next 9 days.
- Continue taking one pill each day at the same time for the rest of your cycle.

Days 18–24

- Do not take any pills from your current blister pack and throw the pack away.
- Take Day 1 pill from a new blister pack.
- Use back-up contraception for the next 9 days.
- Continue taking one pill from the new blister pack at the same time each day.

Days 25–28

- Take your missed pill immediately.
- Take your next pill at the usual time (you may have to take two pills that day).
- No back-up contraception is needed.
- Continue taking one pill each day at the same time for the rest of your cycle.

If you miss TWO PILLS in a row

Days 1–17
(if you miss the pills for Days 17 and 18, follow the instructions for Days 17–25 instead)

- Do not take the missed pills. Instead, take the pill for the day on which you first noticed you had missed pills.
- Use back-up contraception for the next 9 days.
- Continue taking one pill each day at the same time for the rest of your cycle.

Days 17–25
(if you miss the pills for Days 25 and 26, follow the instructions for Days 25–28 instead)

- Do not take any pills from your current blister pack and throw the pack away.
- Take Day 3 pill from a new blister pack.
- Use back-up contraception for the next 9 days.
- Continue taking one pill from the new blister pack at the same time each day.

Days 25–28

- Do not take any pills from your current blister pack and throw the pack away.
- Start a new pack on the same day or start a new pack on the day you usually start a new pack.
- No back-up contraception is needed.
- Continue taking one pill from the new pack at the same time each day, for the rest of your cycle.

You may already be pregnant or COULD BECOME PREGNANT if you had sex on the days after the pills were missed. The more pills missed and the closer they are to the end of the cycle, the higher the risk of a pregnancy. You should call your doctor or healthcare provider if you are unsure whether you are already pregnant.

If you are still not sure of what to do about the pills you have missed:

- Call your healthcare provider
- Use back-up contraception (such as condoms and spermicides) anytime you have sex and keep taking 1 pill each day

Who Should Not Take Estradiol Valerate and Estradiol Valerate/Dienogest?

Your healthcare provider will not give you Estradiol Valerate and Estradiol Valerate/Dienogest if you have:

- Ever had breast cancer or any cancer that is sensitive to female hormones
- Liver disease, including liver tumors
- Ever had blood clots in your arms, legs, or lungs
- Ever had a stroke
- Ever had a heart attack
- Certain heart valve problems or heart rhythm abnormalities that can cause blood clots to form in the heart
- An inherited problem with your blood that makes it clot more than normal
- High blood pressure that medicine can't control
- Diabetes with kidney, eye, or blood vessel damage
- Certain kinds of severe migraine headaches with aura, numbness, weakness or changes in vision

If any of these conditions happen for the first time while using Estradiol Valerate and Estradiol Valerate/Dienogest, stop taking Estradiol Valerate and Estradiol Valerate/Dienogest right away and talk to your healthcare provider. You should use non-hormonal contraceptive measures when you stop using Estradiol Valerate and Estradiol Valerate/Dienogest.

Also, do not take birth control pills if you:

- Smoke and are over 35 years old
- Are pregnant
- Have any unexplained bleeding from the vagina

Birth control pills may not be a good choice for you if you have ever had jaundice (yellowing of the skin or eyes) caused by pregnancy (also called cholestasis of pregnancy).

What Else Should I Know about Taking Estradiol Valerate and Estradiol Valerate/Dienogest?

Birth control pills do not protect you against any sexually transmitted disease, including HIV, the virus that causes AIDS.

Do not skip any pills, even if you do not have sex often.

If you miss a period, you could be pregnant. However, some women miss periods or have light periods on birth control pills, even when they are not pregnant. Contact your healthcare provider for advice if you:

- Think you are pregnant
- Miss one period and have not taken your birth control pills according to directions
- Miss two periods in a row

Birth control pills should not be taken during pregnancy. However, birth control pills taken by accident during pregnancy are not known to cause birth defects.

If you are breastfeeding, consider another birth control method until you are ready to stop breastfeeding. Birth control pills that contain estrogen, like Estradiol Valerate and Estradiol Valerate/Dienogest, may decrease the amount of milk you make. A small amount of the pill's hormones pass into breast milk.

Tell your healthcare provider about all medicines and herbal products that you take. You should not choose Estradiol Valerate and Estradiol Valerate/Dienogest as your birth control pill if you take carbamazepine, phenytoin, rifampicin or St. John's wort, because these medicines may make Estradiol Valerate and Estradiol Valerate/Dienogest ineffective. Some other medicines and herbal products may make birth control pills less effective, including:

- Barbiturates
- Bosentan
- Felbamate
- Griseofulvin
- Oxcarbazepine
- Topiramate

Consider using another birth control method when you take medicines that may make birth control pills less effective.

Birth control pills may interact with lamotrigine, an anticonvulsant used for epilepsy. This may increase the risk of seizures, so your healthcare provider may need to adjust the dose of lamotrigine.

If you have vomiting or diarrhea, your birth control pills may not work as well. Use another birth control method, like condoms and a spermicide, until you check with your healthcare provider.

If you are scheduled for any laboratory tests, tell your healthcare provider you are taking birth-control pills. Certain blood tests may be affected by birth-control pills.

What are the Most Serious Risks of Taking Birth Control Pills?

Like pregnancy, birth control pills increase the risk of serious blood clots, especially in women who have other risk factors, such as smoking, obesity, or age greater than 35. This increased risk is highest when you first start taking birth control pills and when you restart the same or different birth control pills after not using them for a month or more.

It is possible to die from a problem caused by a blood clot, such as a heart attack or a stroke. Some examples of serious blood clots are blood clots in the:

- Legs (deep vein thrombosis)
- Lungs (pulmonary embolus)
- Eyes (loss of eyesight)
- Heart (heart attack)
- Brain (stroke)

A few women who take birth control pills may get:

- High blood pressure
- Gallbladder problems
- Rare cancerous or noncancerous liver tumors
All of these events are uncommon in healthy women.

Call your healthcare provider right away if you have:

- Persistent leg pain
- Sudden shortness of breath
- Sudden blindness, partial or complete
- Severe pain in your chest
- Sudden, severe headache unlike your usual headaches
- Weakness or numbness in an arm or leg, or trouble speaking
- Yellowing of the skin or eyeballs
What are the Common Side Effects of Birth Control Pills?

The most common side effects of birth control pills are:

- Spotting or bleeding between menstrual periods
- Nausea
- Breast tenderness
- Headache

These side effects are usually mild and usually disappear with time.

Less common side effects are:

- Acne
- Less sexual desire
- Bloating or fluid retention
- Blotchy darkening of the skin, especially on the face
- High blood sugar, especially in women who already have diabetes
- High fat levels in the blood
- Depression, especially if you have had depression in the past.

Call your healthcare provider immediately if you have any thoughts of harming yourself.

- Problems tolerating contact lenses
- Weight changes

This is not a complete list of possible side effects. Talk to your healthcare provider if you develop any side effects that concern you. You may report side effects to the FDA at 1-800-FDA-1088.

No serious problems have been reported from a birth control pill overdose, even when accidentally taken by children.

Do Birth Control Pills Cause Cancer?

Birth control pills do not seem to cause breast cancer. However, if you have breast cancer now, or have had it in the past, do not use birth control pills because some breast cancers are sensitive to hormones.

Women who use birth control pills may have a slightly higher chance of getting cervical cancer. However, this may be due to other reasons such as having more sexual partners.

What Should I Know about My Period when Taking Estradiol Valerate and Estradiol Valerate/Dienogest?

Irregular vaginal bleeding or spotting may occur while you are taking Estradiol Valerate and Estradiol Valerate/Dienogest. Irregular bleeding may vary from slight staining between menstrual periods to breakthrough bleeding, which is a flow much like a regular period. Irregular bleeding occurs most often during the first few months of oral contraceptive use, but may also occur after you have been taking the pill for some time. Such bleeding may be temporary and usually does not indicate any serious problems. It is important to continue taking your pills on schedule. If the bleeding occurs in more than one cycle, is unusually heavy, or lasts for more than a few days, call your healthcare provider.

Also, your menstrual period while using oral contraceptives may be shorter and lighter than usual. Some women may not have a menstrual period but this should not be cause for alarm as long has you have taken the pills according to direction.

What if I Miss My Scheduled Period when Taking Estradiol Valerate and Estradiol Valerate/Dienogest?

It is not uncommon to miss your period. However, if you miss more than two periods in a row or miss one period when you have not taken your birth control pills according to directions, call your healthcare provider. Also notify your healthcare provider if you have symptoms of pregnancy such as morning sickness or unusual breast tenderness. It is important that your healthcare provider checks you to find out if you are pregnant. Stop taking Estradiol Valerate and Estradiol Valerate/Dienogest if you are pregnant.

What If I Want to Become Pregnant?

You may stop taking the pill whenever you wish. Consider a visit with your healthcare provider for a pre-pregnancy checkup before you stop taking the pill.

General Advice about Estradiol Valerate and Estradiol Valerate/Dienogest

Your healthcare provider prescribed Estradiol Valerate and Estradiol Valerate/Dienogest for you. Please do not share Natazia with anyone else. Keep Natazia out of the reach of children.

If you have concerns or questions, ask your healthcare provider. You may also ask your healthcare provider for a more detailed label written for medical professionals.

Revised August 2015

Manufactured for:
Bayer HealthCare Pharmaceuticals Inc.
Whippany, NJ 07981
Manufactured in Germany

Distributed by:
Sandoz Inc.
Princeton, NJ 08540

© 2015, Bayer HealthCare Pharmaceuticals Inc.
All Rights Reserved.

PACKAGE/LABEL PRINCIPAL DISPLAY PANEL

Estradiol Valerate and Estradiol Valerate/Dienogest

NDC 0781-4110-52
1 Unit

Rx only

This product (like all oral contraceptives) is
intended to prevent pregnancy. It does not protect
against HIV infection (AIDS) and other sexually
transmitted diseases.

Estradiol Valerate and Estradiol Valerate/Dienogest Tablets
estradiol valerate 3 mg, 1 mg tablets
estradiol valerate/dienogest 2 mg/2 mg, 2mg/3 mg tablets

28 tablets
oral